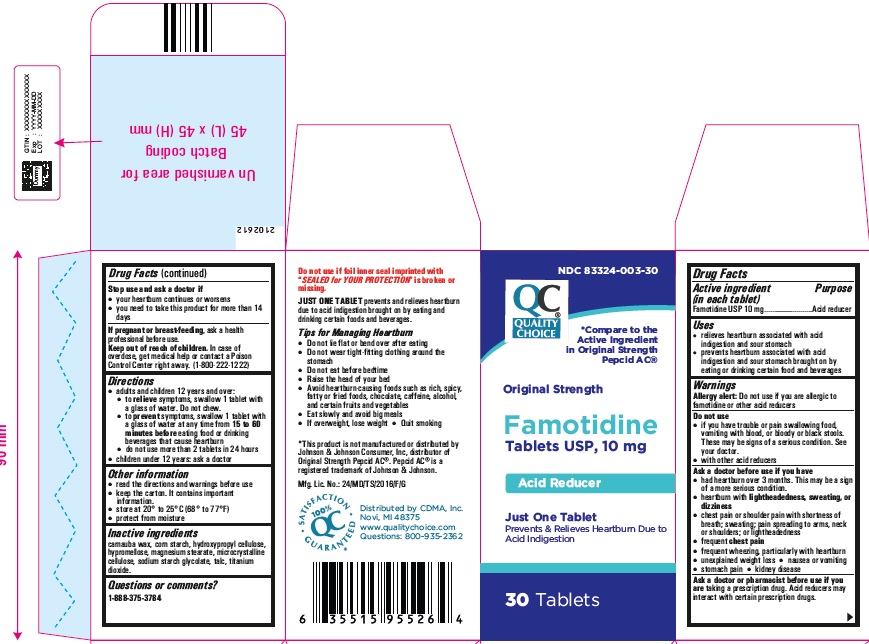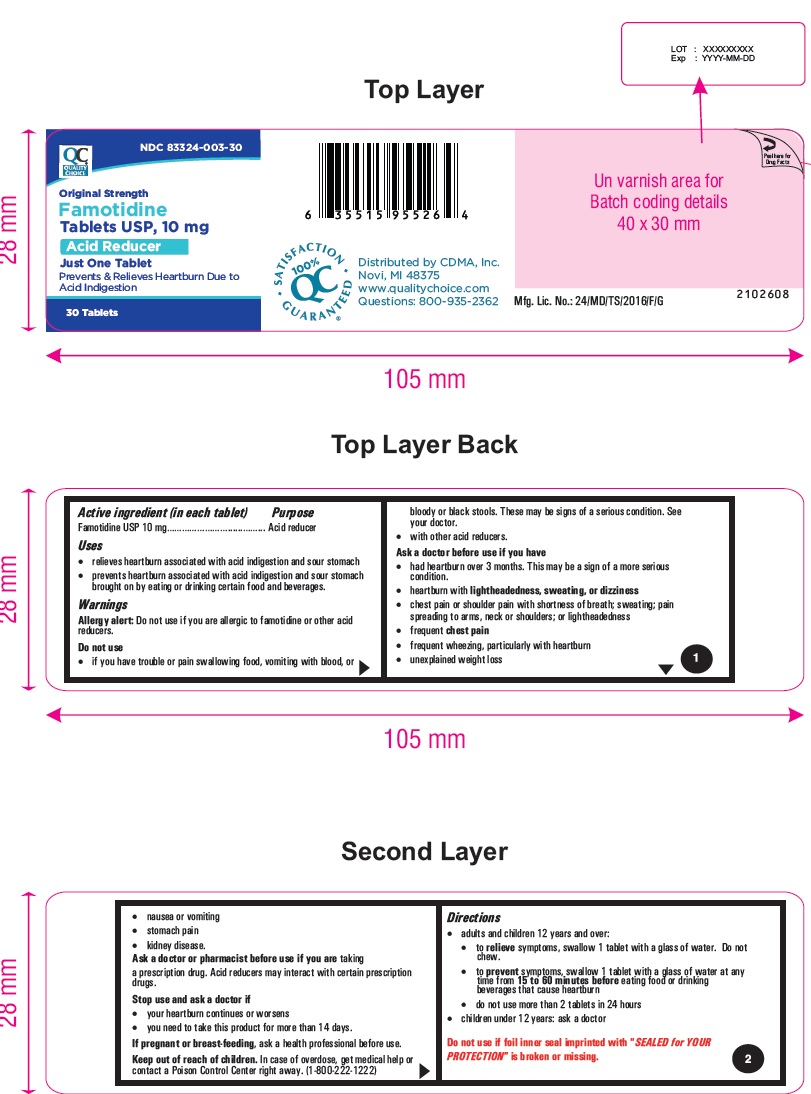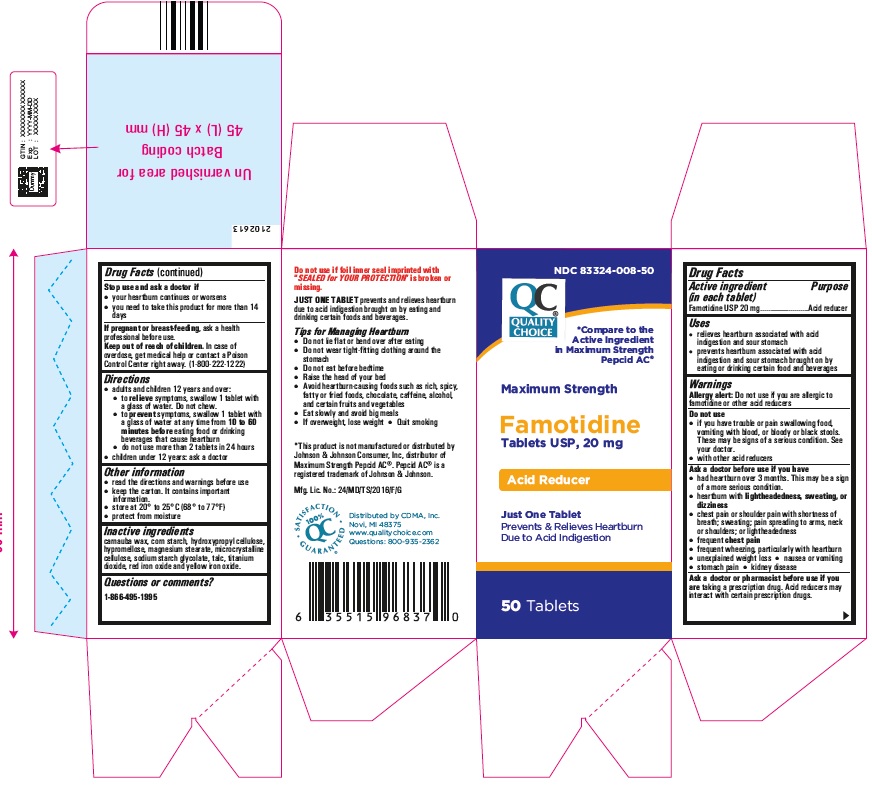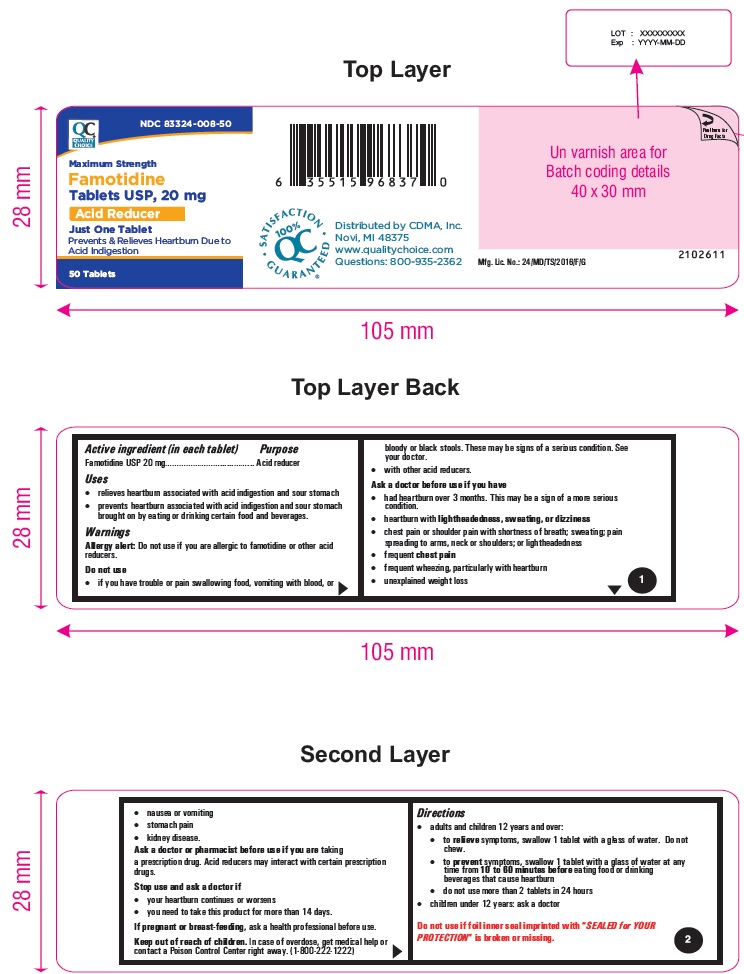 DRUG LABEL: famotidine

NDC: 83324-003 | Form: TABLET, FILM COATED
Manufacturer: CHAIN DRUG MARKETING ASSOCIATION, INC.
Category: otc | Type: HUMAN OTC DRUG LABEL
Date: 20240327

ACTIVE INGREDIENTS: FAMOTIDINE 10 mg/1 1
INACTIVE INGREDIENTS: MAGNESIUM STEARATE; HYPROMELLOSE 2910 (15 MPA.S); MICROCRYSTALLINE CELLULOSE 101; STARCH, CORN; SODIUM STARCH GLYCOLATE TYPE A POTATO; HYPROMELLOSE 2910 (5 MPA.S); MICROCRYSTALLINE CELLULOSE 102; HYDROXYPROPYL CELLULOSE, UNSPECIFIED; TITANIUM DIOXIDE; TALC; CARNAUBA WAX

Famotidine tablets USP, 10 mg and 20 mg

Active ingredient (in each tablet)

Famotidine USP 10 mg and 20 mg

Purpose

Acid reducer

Uses

• relieves heartburn associated with acid indigestion and sour stomach
• prevents heartburn associated with acid indigestion and sour stomach brought on by eating or drinking certain food and beverages

Warnings

Allergy alert:Do not use if you are allergic to famotidine or other acid reducers

Do not use

• if you have trouble or pain swallowing food, vomiting with blood, or bloody or black stools. These may be signs of a serious condition. See your doctor.
• with other acid reducers

Ask a doctor before use if you have

• had heartburn over 3 months. This may be a sign of a more serious condition.
• heartburn with lightheadedness, sweating, or dizziness
• chest pain or shoulder pain with shortness of breath; sweating; pain spreading to arms, neck or shoulders; or lightheadedness
• frequent chest pain
• frequent wheezing, particularly with heartburn
• unexplained weight loss
• nausea or vomiting
• stomach pain
• kidney disease

Ask a doctor or pharmacist before use if you are

taking a prescription drug. Acid reducers may interact with certain prescription drugs.

Stop use and ask a doctor if

• your heartburn continues or worsens
• you need to take this product for more than 14 days

If pregnant or breast-feeding,

ask a health professional before use.

Keep out of reach of children.

In case of overdose, get medical help or contact a Poison Control Center right away. (1-800-222-1222)

Directions

• adults and children 12 years and over:
• to relievesymptoms, swallow 1 tablet with a glass of water. Do not chew.

10 mg:
• to preventsymptoms, swallow 1 tablet with a glass of water at any time from 15 to 60 minutes beforeeating food or drinking beverages that cause heartburn

20 mg:

• to preventsymptoms, swallow 1 tablet with a glass of water at any time from 10 to 60 minutes beforeeating food or drinking beverages that cause heartburn

• do not use more than 2 tablets in 24 hours
• children under 12 years: ask a doctor

Other information

• read the directions and warnings before use
• keep the carton. It contains important information.
• store at 20° to 25°C (68° to 77°F)
• protect from moisture

Inactive ingredients

10 mg:
carnauba wax, corn starch, hydroxypropyl cellulose, hypromellose, magnesium stearate, microcrystalline cellulose, sodium starch glycolate, talc, titanium dioxide.

20 mg:

carnauba wax, corn starch, hydroxypropyl cellulose, hypromellose, magnesium stearate, microcrystalline cellulose, sodium starch glycolate, talc, titanium dioxide, red iron oxide and yellow iron oxide.

Questions or comments?

1-888-375-3784
JUST ONE TABLET prevents and relieves heartburn due to acid indigestion brought on by eating and drinking certain foods and beverages.
Tips for Managing Heartburn
· Do not lie flat or bend over after eating
· Do not wear tight-fitting clothing around the stomach
· Do not eat before bedtime
· Raise the head of your bed
· Avoid heartburn-causing foods such as rich, spicy, fatty or fried foods, chocolate, caffeine, alcohol, and certain fruits and vegetables
· Eat slowly and avoid big meals
· If overweight, lose weight
· Quit smoking

Distributed by CDMA, Inc.
Novi, MI 48375
www.qualitychoice.com
Questions: 800-935-2362

PRINCIPAL DISPLAY PANEL

Famotidine Tablets USP 10 mg - 30s container label

Famotidine Tablets USP 10 mg - 30s container carton label

Famotidine Tablets USP 20 mg - 50s container label

Famotidine Tablets USP 20 mg - 50s container carton label